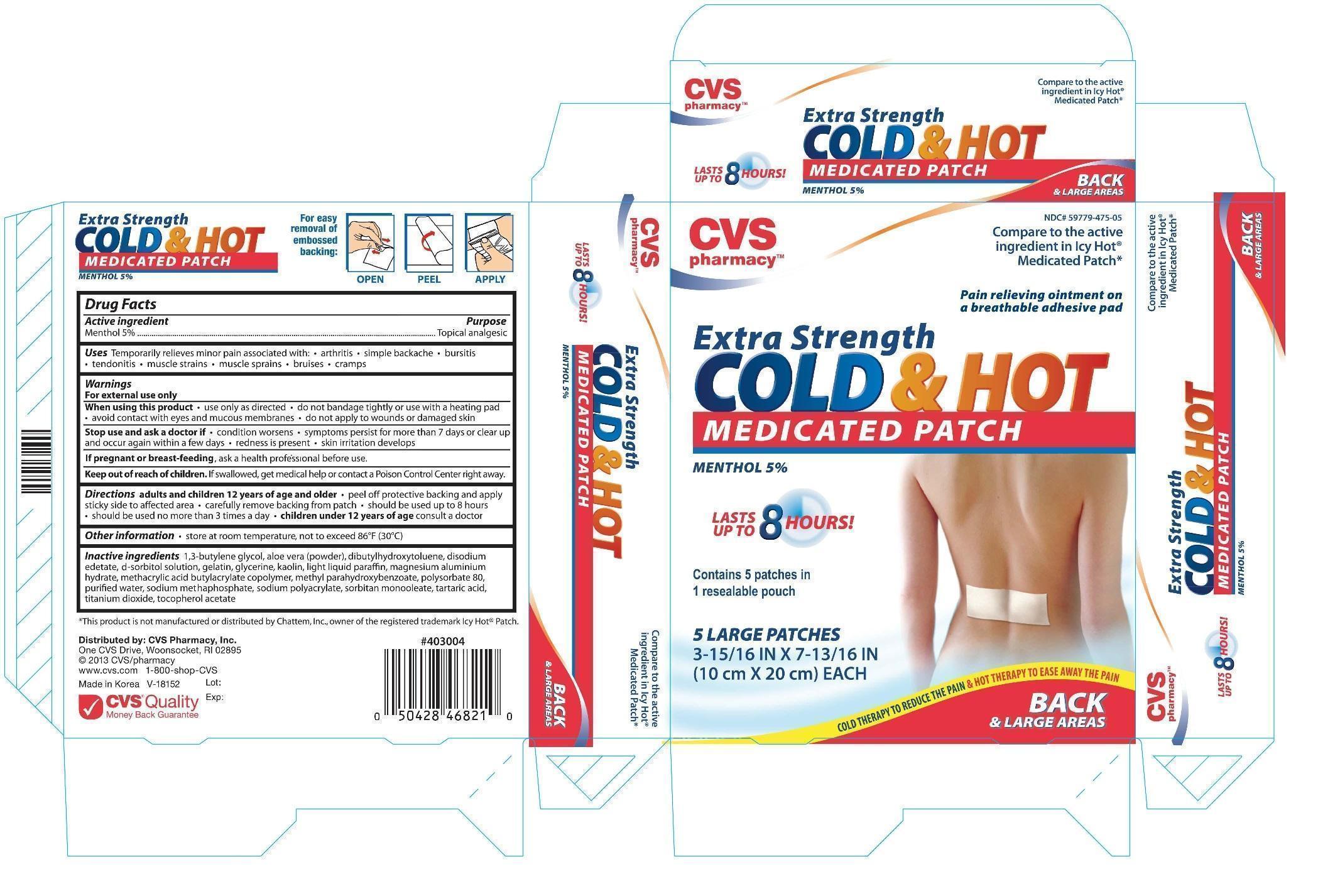 DRUG LABEL: CVS Cold Hot Medicated
NDC: 59779-821 | Form: PATCH
Manufacturer: CVS Pharmacy Inc.
Category: otc | Type: HUMAN OTC DRUG LABEL
Date: 20131014

ACTIVE INGREDIENTS: MENTHOL 0.05 g/1 g
INACTIVE INGREDIENTS: 1,3-BUTYLENE GLYCOL; ALOE VERA FLOWER; GELATIN; GLYCERIN; KAOLIN; PARAFFIN; MAGNESIUM ALUMINUM SILICATE; POLYSORBATE 80; WATER; SODIUM POLYACRYLATE (8000 MW); SORBITAN MONOOLEATE; TARTARIC ACID; TITANIUM DIOXIDE; ALPHA-TOCOPHEROL ACETATE

Drug Facts

Active Ingredient Purpose

Menthol 5% .......................................................Topical Analgesic

Uses

Temporarily relieves minor pain associated with:

- Arthritis
- Simple Backache
- Bursitis
- Tendonitis
- Muscle Strains
- Bruises
- Cramps

WARNINGS

For external use only

When using this product

- Use only as directed
- Do not bandage tightly or use with a heating pad
- Avoid contact with eyes and mucous membranes
- Do not apply to wounds or damaged skin

Stop use and ask a doctor if

- Condition worsens
- Symptoms persist for more than 7 days or clear up and occur again within a few days
- Redness is present
- Skin irritation develops

PREGNANCY OR BREAST FEEDING

If pregnant or breast-feeding, ask a health professional before use.

Keep out of reach of children. If swallowed, get medical help or contact a Poision Control Center right away.

INDICATIONS AND USAGE

Directions: adults and children 12 years of age and older

- Peel off protective backing and apply sticky side to affected area
- Carefully remove backing from patch
- Should be used up to 8 hours
- Should be used no more than 3 times a day
- Children under 12 years of age consult a doctor

Other Information

- Store at room temperature, not to exceed 86° (30°C)

Inactive Ingredients:

1,3 butylene glycol, aloe vera (powder), dibutylhydroxytoluene, disodium edetate, d-sorbital solution, glycerine, kaolin, light liquid paraffin, magnesium aluminum hydrate, methacrylic acid butylacrylate copolymer, methyl parahydroxybenzoate, polysorbate 80, purified water, sodium methaphosphate, sodium polyacrylate, sorbitan monooleate, tartaric acid, titanium dioxide, tocopherol acetate

DOSAGE AND ADMINISTRATION

DISTRIBUTED BY:

CVS PHARMACY, INC.

ONE CVS DRIVE

WOONSOCKET, RI 02895 USA